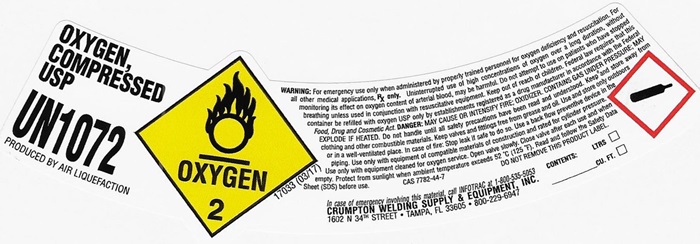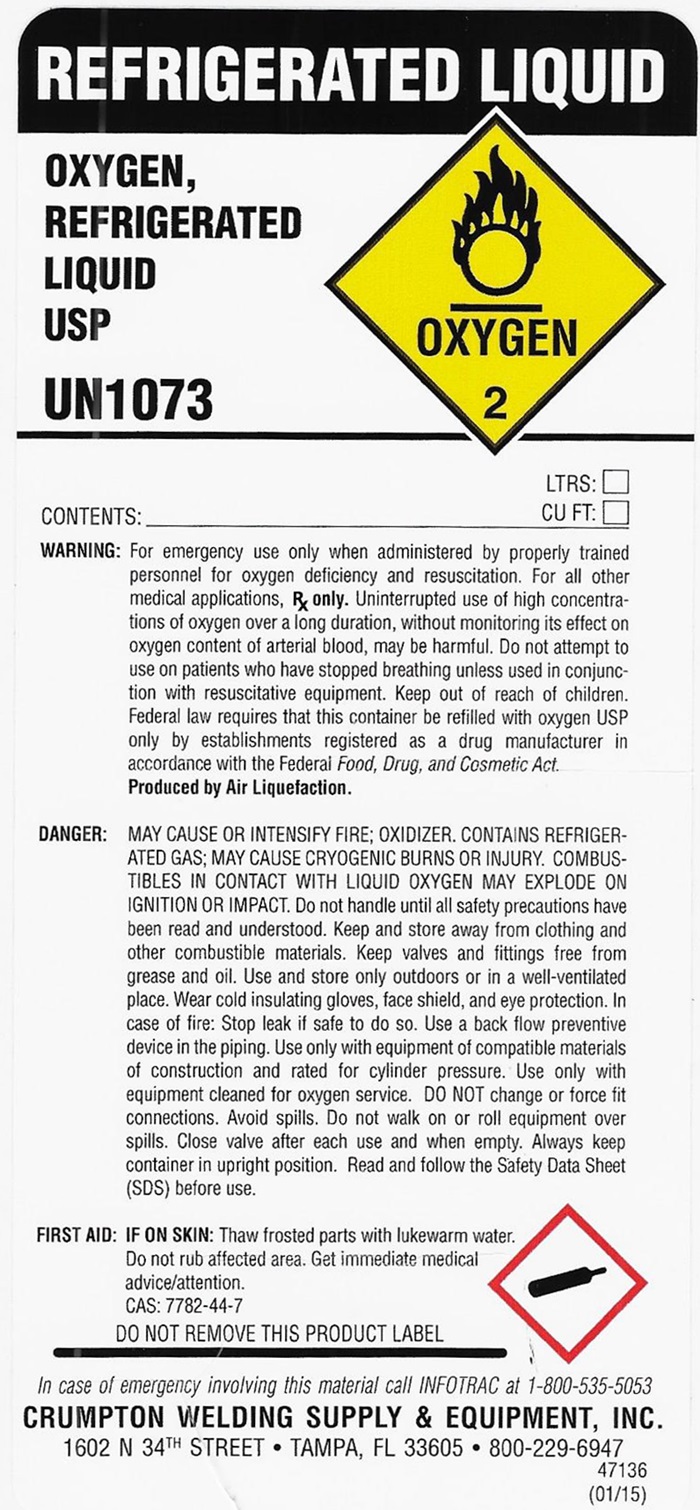 DRUG LABEL: OXYGEN
NDC: 52568-001 | Form: GAS
Manufacturer: Crumpton Welding Supply & Equipment, Inc.
Category: prescription | Type: HUMAN PRESCRIPTION DRUG LABEL
Date: 20250210

ACTIVE INGREDIENTS: OXYGEN 99 L/100 L

Oxygen

OXYGEN COMPRESSED LABEL

OXYGEN, COMPRESSED USP UN 1072 Produced by Air Liquefaction OXYGEN 2 17033 (03/17)

WARNING: For emergency use only when administered by properly trained personnel for oxygen deficiency and resuscitation. For all other medical applications, Rx only. Uninterrupted use of high concentrations of oxygen over a long duration, without monitoring its effect on oxygen content of arterial blood, may be harmful. Do not attempt to use on patients who have stopped breathing unless used in conjunction with resuscitative equipment. DANGER: MAY CAUSE OR INTENSIFY FIRE; OXIDIZER. CONTAINS GAS UNDER PRESSURE; MAY EXPLODE IF HEATED. Do not handle until all safety precautions have been read and understood. Keep and store away from clothing and other combustible materials. Keep valves and fittings free from grease and oil. Use and store only outdoors or in a well-ventilated place. In case of fire: Stop leak if safe to do so. Use a backflow preventive device in the piping. Use only with equipment of compatible materials of construction and rated for cylinder pressure. Use only with equipment cleaned for oxygen service. Open valve slowly. Close valve after each use and when empty. Protect from sunlight when ambient temperature exceeds 52°C (125° F). Read and follow the Safety Data Sheet (SDS) before use. CAS 7782-44-7 DO NOT REMOVE THIS PRODUCT LABEL.

CONTENTS:

LTRS: ___

CU.FT. ___

In case of emergency involving this material call INFOTRAC at 1-800-535-5063

CRUMPTON WELDING SUPPLY & EQUIPMENT, INC.

1602 N 34TH STREET • TAMPA, FL 33605 • 800-229-6947

REFRIGERATED LIQUID LABEL

REFRIGERATED LIQUID

OXYGEN, REFRIGERATED LIQUID USP UN1073

OXYGEN 2

CONTENTS: __________________ LTRS: ___ CU.FT. ___

WARNING: For emergency use only when administered by properly trained personnel for oxygen deficiency and resuscitation. For all other medical applications, Rx only.

Uninterrupted use of high concentrations of oxygen over a long duration, without monitoring its effect on oxygen content of arterial blood, may be harmful. Do not attempt to use on patients who have stopped breathing unless used in conjunction of resuscitative equipment. Keep out of reach of children.

Federal law requires that this container be refilled with oxygen USP only by establishments registered as a drug manufacturer in accordance with the Federal Food, Drug, and Cosmetic Act.

Produced by Air Liquefaction.

DANGER: MAY CAUSE OR INTENSIFY FIRE; OXIDER, CONTAINS REFRIGERATED GAS; MAY CAUSE CRYOGENIC BURNS OR INJURY. COMBUSTIBELS IN CONTACT WITH LIQUID OXYGEN MAY EXPLODE ON IGNITION OR IMPACT.

Do not handle until all safety precautions have been read and understood. Keep and store away from clothing and other combustible materials. Keep valves and fittings free from grease and oil. Use and store only outdoors or in a well-ventilated place. Wear cold insulating gloves, face shield, and eye protection. In case of fire: Stop leak if safe to do so. Use a back flow preventive device in the piping. Use only the equipment of compatible materials equipment cleaned for oxygen service. DO NOT change or force fit connections. Avoid spills. Do not walk on or roll equipment over spills. Close valve after each use and when empty. Always keep container in upright position. Read and follow the Safety Data Sheet (SDS) before use.

FIRST AID FIRST AID: IF ON SKIN: Thaw affected parts with lukewarm water. Do not rub affected area. Get immediate medical advice/attention. CAS: 7782-44-7

DO NOT REMOVE THIS PRODUCT LABEL

In case of emergency involving this material call INFOTRAC at 1-800-535-5063

CRUMPTON WELDING SUPPLY & EQUIPMENT, INC.

1602 N 34TH STREET • TAMPA, FL 33605 • 800-229-6947

47136 (01/15)